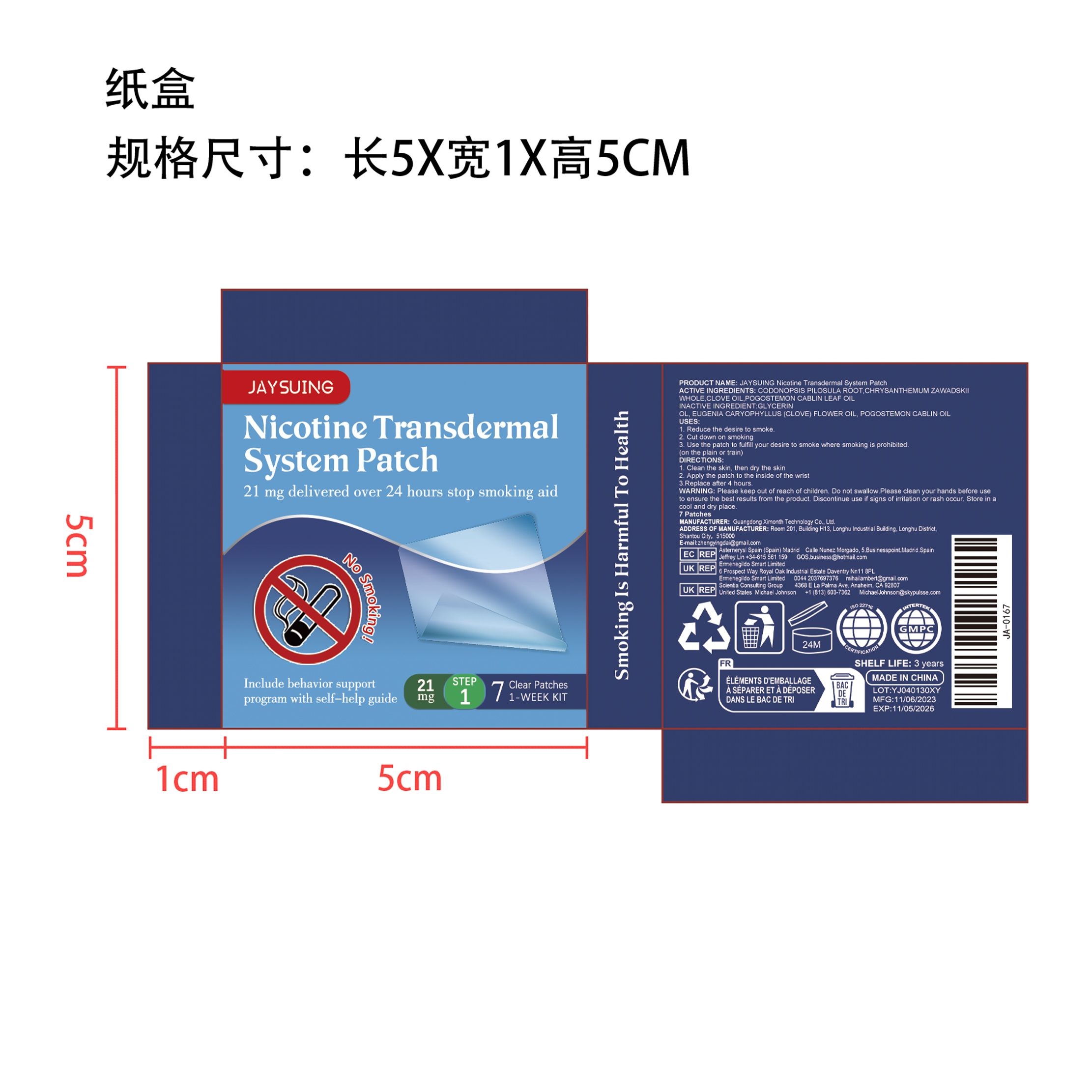 DRUG LABEL: JAYSUING Nicotine Transdermal System Patch
NDC: 84660-068 | Form: PATCH
Manufacturer: Guangdong Ximonth Technology Co., Ltd.
Category: otc | Type: HUMAN OTC DRUG LABEL
Date: 20241104

ACTIVE INGREDIENTS: CLOVE OIL 0.75 g/5 g; CODONOPSIS PILOSULA ROOT 1.5 g/5 g; CHRYSANTHEMUM ZAWADSKII WHOLE 0.5 g/5 g; POGOSTEMON CABLIN LEAF OIL 0.75 g/5 g
INACTIVE INGREDIENTS: GLYCERIN 1.5 g/5 g

ACTIVE INGREDIENTS

CODONOPSIS PILOSULA ROOT,CHRYSANTHEMUM ZAWADSKII WHOLE,CLOVE OIL,POGOSTEMON CABLIN LEAF OIL

PURPOSE

1. Reduce the desire to smoke. 2. Cut down on smoking3. Use the patch to fulfill your desire to smoke where smoking is prohibited. (on the plain or train)

USES

1. Clean the skin, then dry the skin2. Apply the patch to the inside of the wrist3.Replace after 4 hours.

WARNINGS

Please keep out of reach of children. Do not swallow. Please clean your hands before use to ensure the best results from the product. Discontinue use if signs of irritation or rash occur. Store in a cool and dry place.

STOP USE

Discontinue use if signs of irritation or rash occur.

DO NOT USE

Discontinue use if signs of irritation or rash occur.

KEEP OUT OF REACH OF CHILDREN

Please keep out of reach of children. Do not swallow.

STORAGE AND HANDLING

Store in a cool and dry place.

INACTIVE INGREDIENT

GLYCERIN